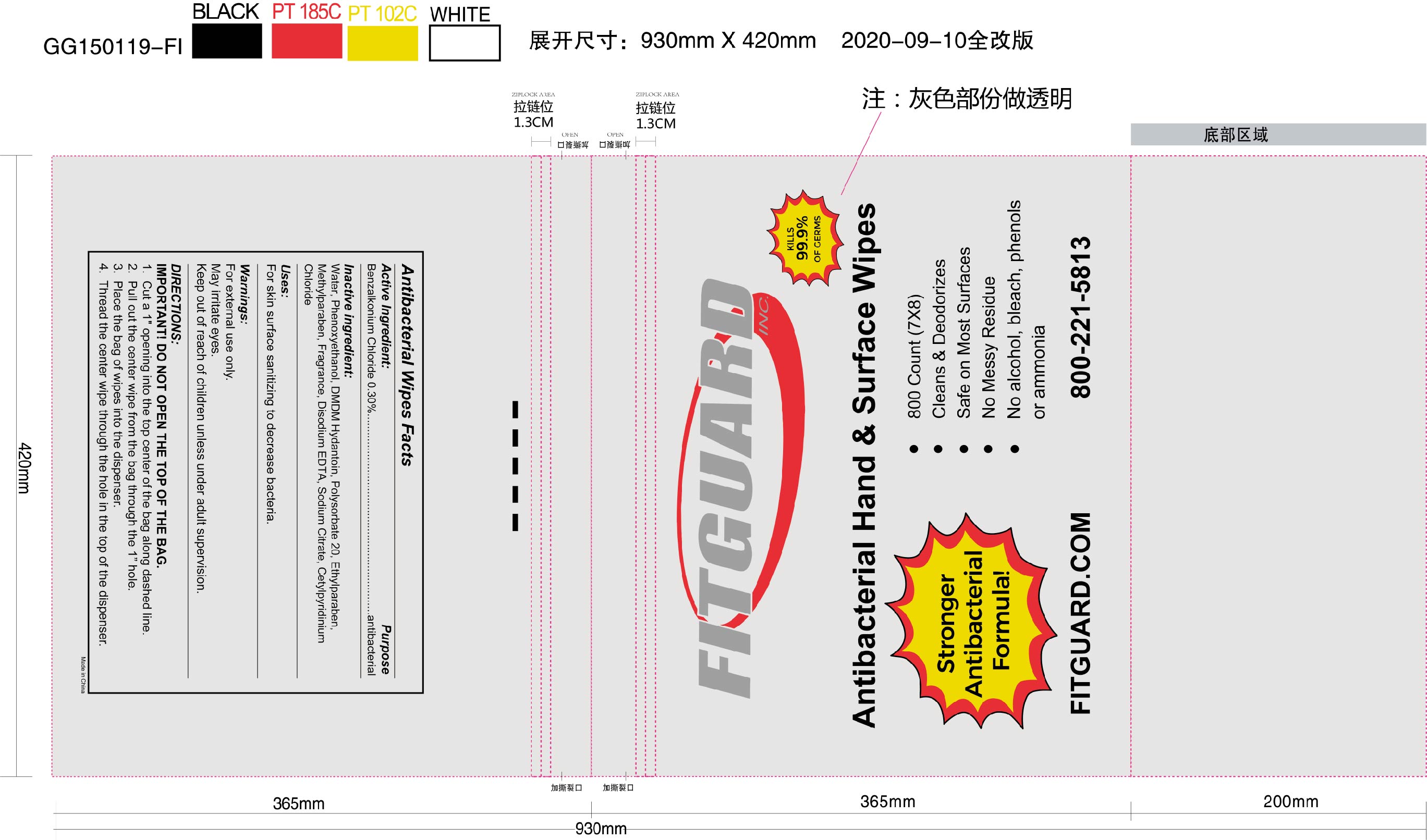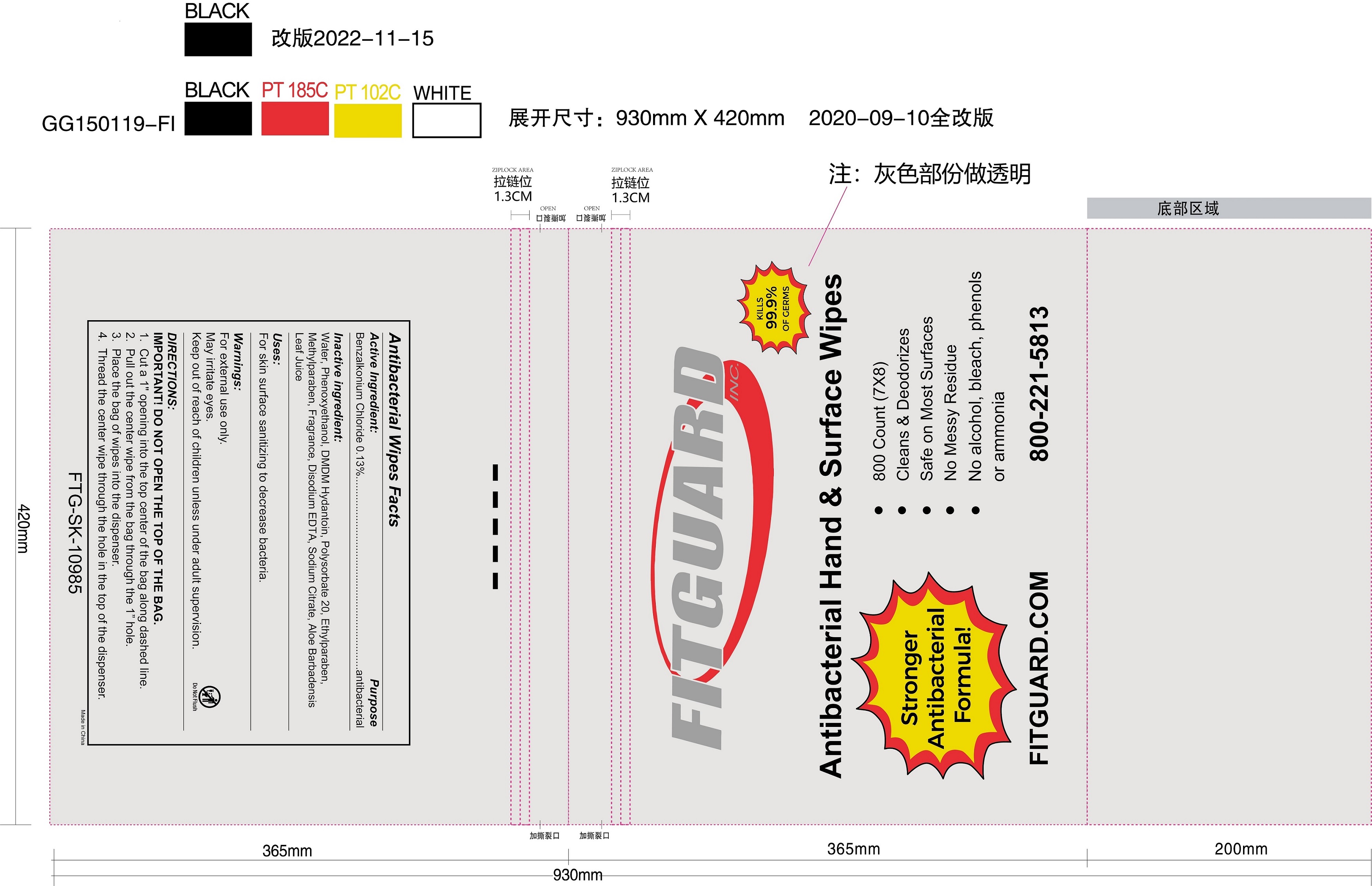 DRUG LABEL: Antibacterial Wipes
NDC: 78494-003 | Form: CLOTH
Manufacturer: Fitguard
Category: otc | Type: HUMAN OTC DRUG LABEL
Date: 20221209

ACTIVE INGREDIENTS: BENZALKONIUM CHLORIDE 0.13 mg/1 1
INACTIVE INGREDIENTS: SODIUM CITRATE 0.02 mg/1 1; DMDM HYDANTOIN 0.275 mg/1 1; ETHYLPARABEN 0.09 mg/1 1; METHYLPARABEN 0.06 mg/1 1; WATER 98.724 mg/1 1; PHENOXYETHANOL 0.45 mg/1 1; DISODIUM EDTA-COPPER 0.02 mg/1 1; POLYSORBATE 20 0.2 mg/1 1; ALOE VERA LEAF 0.001 mg/1 1; FRAGRANCE 13576 0.03 mg/1 1

Fitguard Antibacterial Hand Wipes

Purpose

Antibacterial

Active Ingredient:

Benzalkonium Chloride 0.30%

Inactive Ingredients:

Water, Phenoxyethanol, DMDM Hydantoin, Polysorbate 20, Ethylparaben, Methylparaben, Fragrance, Disodium EDTA, Sodium Citrate, Cetylpyridinium Chloride

Uses:

For skin surface sanitizing to decrease bacteria.

Warnings:

For external use only.

May irritate eyes.

Keep out of reach of children unless under adult supervision.

Warnings:

Keep out of reach of children unless under adult supervision.

Directions:

Important! Do not open the top of the bag.

1. Cut a 1" opening into the top center of the bag along dashed line.

2. Pull out the center wipe from the bag through the 1" hole.

3. Place the bag of wipes into the dispenser.

4. Thread the center wipe through the hole in the top of the dispenser.

Instructions for use:

Take single sheets as needed and apply topically to clean skin.